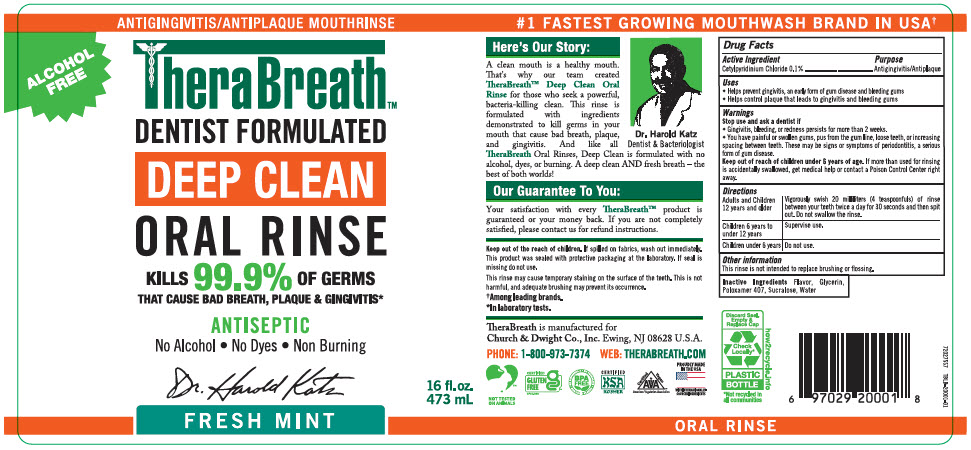 DRUG LABEL: Therabreath Deep Clean Fresh Mint
NDC: 10237-261 | Form: RINSE
Manufacturer: Church & Dwight Co., Inc.
Category: otc | Type: HUMAN OTC DRUG LABEL
Date: 20251205

ACTIVE INGREDIENTS: CETYLPYRIDINIUM CHLORIDE 20 mg/20 mL
INACTIVE INGREDIENTS: WATER; GLYCERIN; POLOXAMER 407; SUCRALOSE

Therabreath™Deep Clean Fresh Mint

Drug Facts

Active Ingredients

Cetylpyridinium Chloride 0.1%

Purpose

Antigingivitis/Antiplaque

Uses

- Helps prevent gingivitis, an early form of gum disease and bleeding gums
- Helps control plaque that leads to gingivitis and bleeding gums

Warnings

Stop use and ask a dentist if

- Gingivitis, bleeding, or redness persists for more than 2 weeks.
- You have painful or swollen gums, pus from the gum line, loose teeth, or increasing spacing between teeth. These may be signs or symptoms of periodontitis, a serious form of gum disease.

Keep out of reach of children under 6 years of age.If more than used for rinsing is accidentally swallowed, get medical help or contact a Poison Control Center right away.

Directions

Adults and Children 12 years and older | Vigorously swish 20 milliliters (4 teaspoonfuls) of rinse between your teeth twice a day for 30 seconds and then spit out. Do not swallow the rinse.
Children 6 years to under 12 years | Supervise use.
Children under 6 years | Do not use.

Other information

This rinse is not intended to replace brushing or flossing.

Inactive Ingredients

Flavor, Glycerin, Poloxamer 407, Sucralose, Water

PRINCIPAL DISPLAY PANEL - 473 mL Bottle Label

ALCOHOL
FREE

ANTIGINGIVITIS/ANTIPLAQUE MOUTHRINSE

TheraBreath™

DENTIST FORMULATED

DEEP CLEAN

ORAL RINSE

KILLS 99.9% OF GERMS
THAT CAUSE BAD BREATH, PLAQUE & GINGIVITIS*

ANTISEPTIC

No Alcohol • No Dyes • Non Burning

FRESH MINT

16 fl.oz.
473 mL